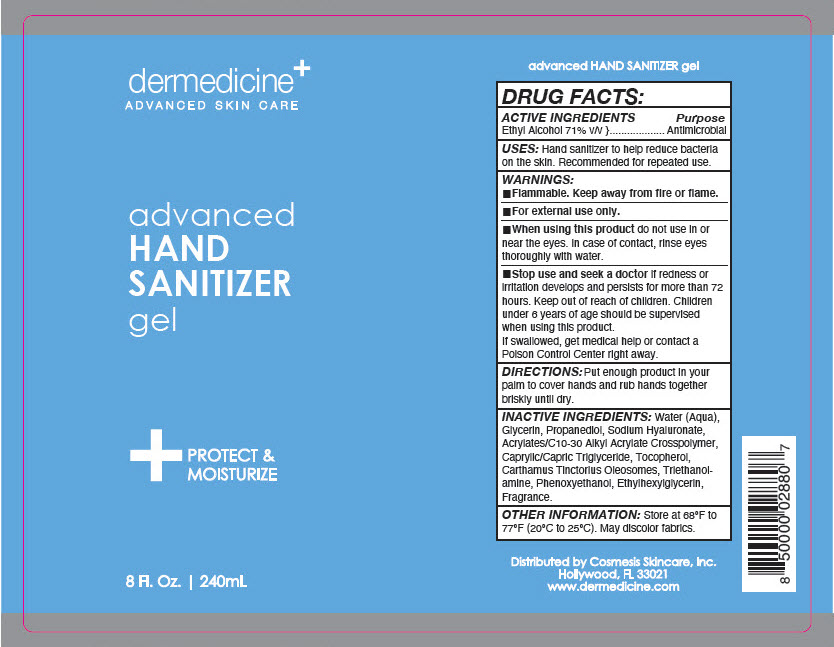 DRUG LABEL: Dermedicine - Advanced Hand Sanitizer
NDC: 66163-1503 | Form: GEL
Manufacturer: Cosmetic Solutions LLC
Category: otc | Type: HUMAN OTC DRUG LABEL
Date: 20200505

ACTIVE INGREDIENTS: ALCOHOL 71 mL/100 mL
INACTIVE INGREDIENTS: WATER; GLYCERIN; PROPANEDIOL; HYALURONATE SODIUM; CARBOMER INTERPOLYMER TYPE A (ALLYL SUCROSE CROSSLINKED); MEDIUM-CHAIN TRIGLYCERIDES; TOCOPHEROL; CARTHAMUS TINCTORIUS SEED OLEOSOMES; TROLAMINE; PHENOXYETHANOL; ETHYLHEXYLGLYCERIN

Dermedicine^+ - Advanced Hand Sanitizer Gel

DRUG FACTS:

ACTIVE INGREDIENTS

Ethyl Alcohol 71% v/v

Purpose

Antimicrobial

USES

Hand sanitizer to help reduce bacteria on the skin. Recommended for repeated use.

WARNINGS

- Flammable. Keep away from fire or flame.

- For external use only.

- When using this product do not use in or near the eyes. In case of contact, rinse eyes thoroughly with water.

- Stop use and seek a doctor if redness or irritation develops and persists for more than 72 hours.

Keep out of reach of children. Children under 6 years of age should be supervised when using this product.

If swallowed, get medical help or contact a Poison Control Center right away.

DIRECTIONS

Put enough product in your palm to cover hands and rub hands together briskly until dry.

INACTIVE INGREDIENTS

Water (Aqua), Glycerin, Propanediol, Sodium Hyaluronate, Acrylates/C10-30 Alkyl Acrylate Crosspolymer, Caprylic/Capric Triglyceride, Tocopherol, Carthamus Tinctorius Oleosomes, Triethanolamine, Phenoxyethanol, Ethylhexylglycerin, Fragrance.

OTHER INFORMATION

Store at 68ºF to 77ºF (20ºC to 25ºC). May discolor fabrics.

Distributed by Cosmesis Skincare, Inc.
Hollywood, FL 33021

PRINCIPAL DISPLAY PANEL - 240 mL Bottle Label

dermedicine^+
ADVANCED SKIN CARE

advanced
HAND
SANITIZER
gel

+
PROTECT &
MOISTURIZE

8 Fl. Oz. | 240mL